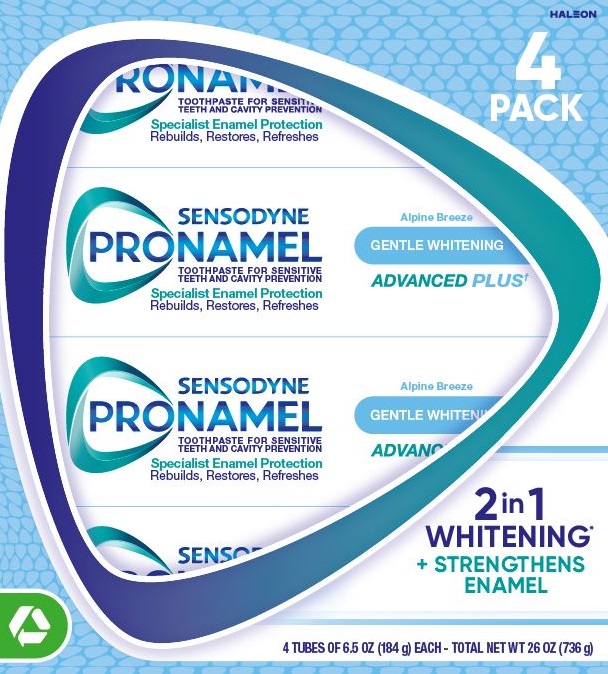 DRUG LABEL: Sensodyne

NDC: 0135-5030 | Form: PASTE
Manufacturer: Haleon US Holdings LLC
Category: otc | Type: HUMAN OTC DRUG LABEL
Date: 20240829

ACTIVE INGREDIENTS: POTASSIUM NITRATE 50 mg/1 g; SODIUM FLUORIDE 1.11 mg/1 g
INACTIVE INGREDIENTS: WATER; SORBITOL; HYDRATED SILICA; GLYCERIN; COCAMIDOPROPYL BETAINE; XANTHAN GUM; TITANIUM DIOXIDE; SACCHARIN SODIUM; SODIUM HYDROXIDE

Drug Facts

Active ingredients

Potassium nitrate 5%

Sodium fluoride 0.25% (0.15% w/v fluoride ion)

Purposes

Antihypersensitivity

Anticavity

Uses

- builds increasing protection against painful sensitivity of the teeth to cold, heat, acids, sweets, or contact.
- aids in the prevention of dental cavities.

Warnings

Stop use and ask a dentist if

- the problem persists or worsens. Sensitive teeth may indicate a serious problem that may need prompt care by a dentist.
- pain/sensitivity still persists after 4 weeks of use.

Keep out of reach of children.

If more than used for brushing is accidentally swallowed, get medical help or contact a Poison Control Center right away.

Directions

- adults and children 12 years of age and older:
  - apply at least a 1-inch strip of the product onto a soft bristle toothbrush.
  - brush teeth thoroughly for at least 1 minute twice a day (morning and evening), and not more than 3 times a day, or as recommended by a dentist or doctor. Make sure to brush all sensitive areas of the teeth. Minimize swallowing. Spit out after brushing.
- children under 12 years of age:Consult a dentist or doctor.

Other information

- do not store above 25°C (77°F)

Inactive ingredients

water, sorbitol, hydrated silica, glycerin, cocamidopropyl betaine, flavor, xanthan gum, titanium dioxide, sodium saccharin, sodium hydroxide

Questions or comments?

1-866-844-2797

Principal Display Panel

HALEON

4 PACK

SENSODYNE PRONAMEL

TOOTHPASTE FOR SENSITIVE TEETH AND CAVITY PREVENTION

Specialist Enamel Protection

Rebuilds, Restores, Refreshes

Alpine Breeze

GENTLE WHITENING

ADVANCED PLUS†

2 in 1 WHITENING*

+ STRENGTHENS ENAMEL

4 TUBES OF 6.5 OZ (184 g) EACH – TOTAL NET WT 26 OZ (736 g)

62000000209634 Carton Front